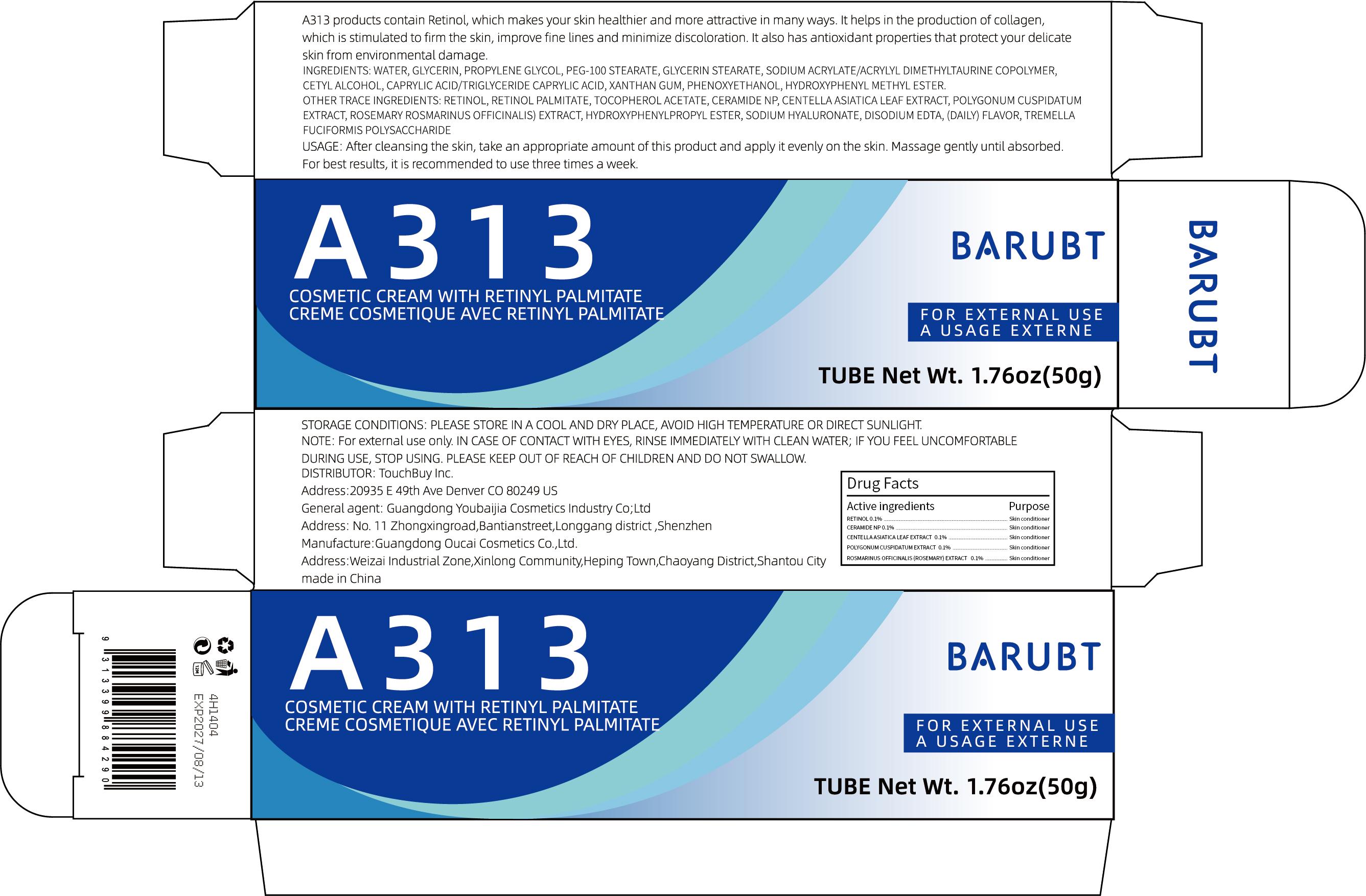 DRUG LABEL: BARUBT A313 Cosmetic Cream With Retinyl Palmitate
NDC: 84712-024 | Form: CREAM
Manufacturer: Guangdong Youbaijia Cosmetic Industry Co., Ltd
Category: otc | Type: HUMAN OTC DRUG LABEL
Date: 20240918

ACTIVE INGREDIENTS: POLYGONUM CUSPIDATUM LEAF 0.05 g/50 g; CENTELLA ASIATICA LEAF 0.05 g/50 g; RETINOL 0.05 g/50 g; CERAMIDE NP 0.05 g/50 g; ROSMARINUS OFFICINALIS FLOWER 0.05 g/50 g
INACTIVE INGREDIENTS: PROPYLENE GLYCOL 1.5 g/50 g; GLYCERIN 2.5 g/50 g

ACTIVE INGREDIENT

RETINOL 0.1%
CERAMIDE NP 0.1%
CENTELLA ASIATICA LEAF EXTRACT 0.1%
POLYGONUM CUSPIDATUM EXTRACT 0.1%
ROSMARINUS OFFICINALIS (ROSEMARY) EXTRACT 0.1%

INACTIVE INGREDIENT

AQUA
GLYCERIN
PROPYLENE GLYCOL
PEG-100 STEARATE
GLYCERYL STEARATE
SODIUM ACRYLATE/SODIUM ACRYLOYLDIMETHYL TAURATE COPOLYMER
CETEARYL ALCOHOL
CAPRYLIC/CAPRIC TRIGLYCERIDE
XANTHAN GUM
PHENOXYETHANOL
METHYLPARABEN
RETINYL PALMITATE
TOCOPHERYL ACETATE
PROPYLPARABEN
SODIUM HYALURONATE
DISODIUM EDTA
FRAGRANCE
TREMELLA FUCIFORMIS POLYSACCHARIDE

Do not use on damaged skin.

Keep away from children. Do not swallow.

PURPOSE

improve fine lines and minimize discoloration

QUESTIONS

Contact name: Jessie Peng
Company phone number: +1 818 579 7288
Company e-mail: jessie@registeragentllc.com

STOP USE

lf skin becomes red or irritated, discontinue use immediately and wash with water.

WHEN USING

keep out of eyes. Rinse with water to remove.

WARNINGS

For external use only.

STORAGE AND HANDLING

PLEASE STORE IN A COOL AND DRY PLACE, AVOID HIGH TEMPERATURE OR DIRECT SUNLIGHT.

INDICATIONS AND USAGE

A313 products contain Retinol, which makes vour skin healthier and more attractive in manv wavs. it helos in the orocucion of colagen.which is stimulated to firm the skin, improve fine lines and minimize discoloration. it also has antioxidant properties that protect your delicate skin from environmental damage

DOSAGE AND ADMINISTRATION

After cleansing the skin, take an appropriate amount of this product and apply it evenly on the skin. Massage gently until absorbed.
For best results,it is recommended to use three times a week.